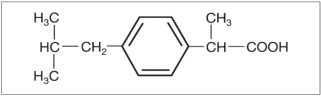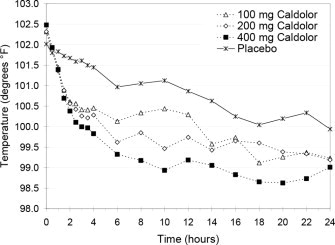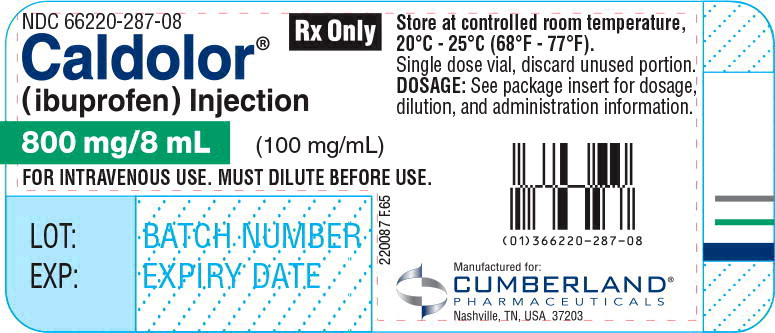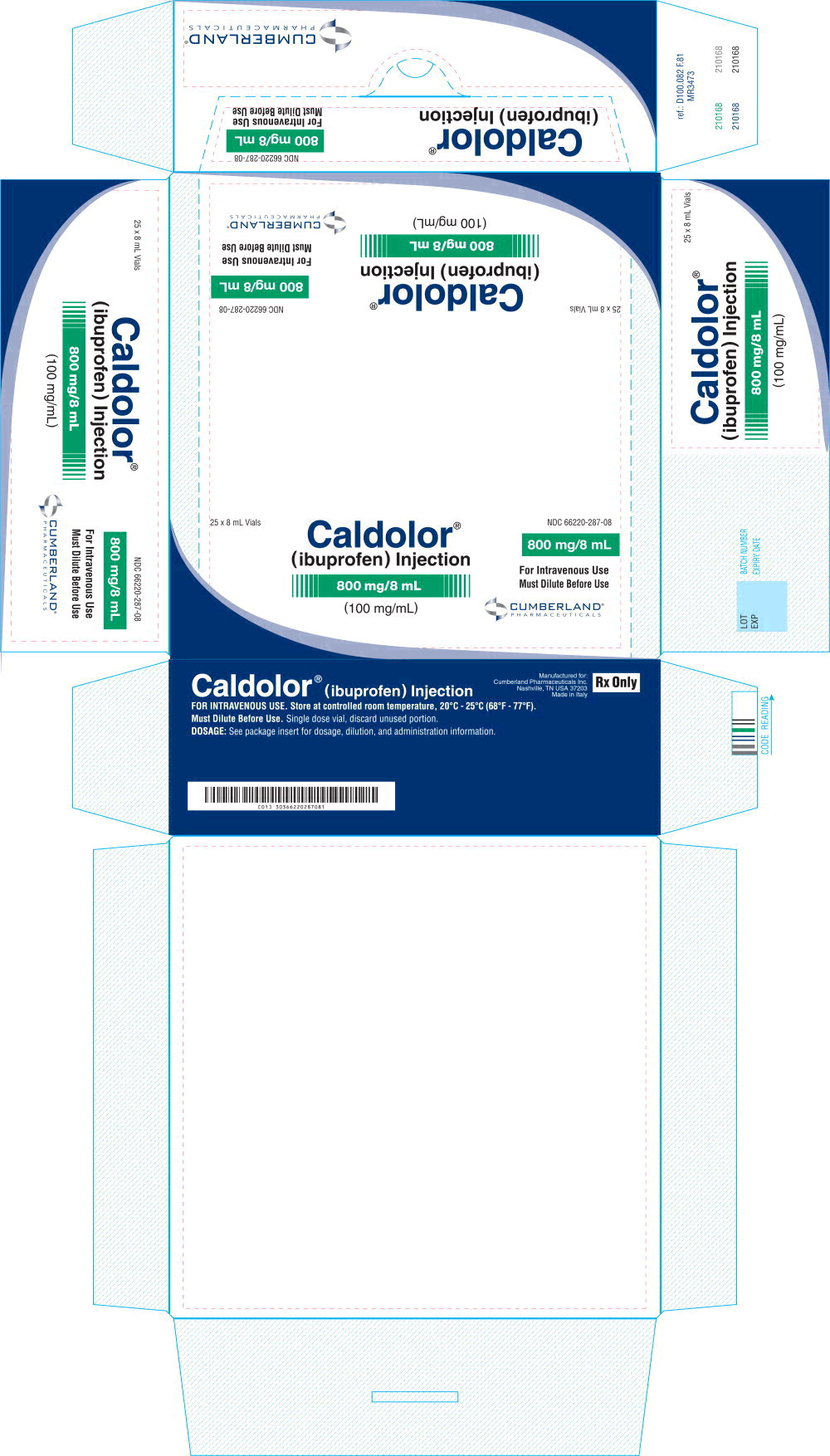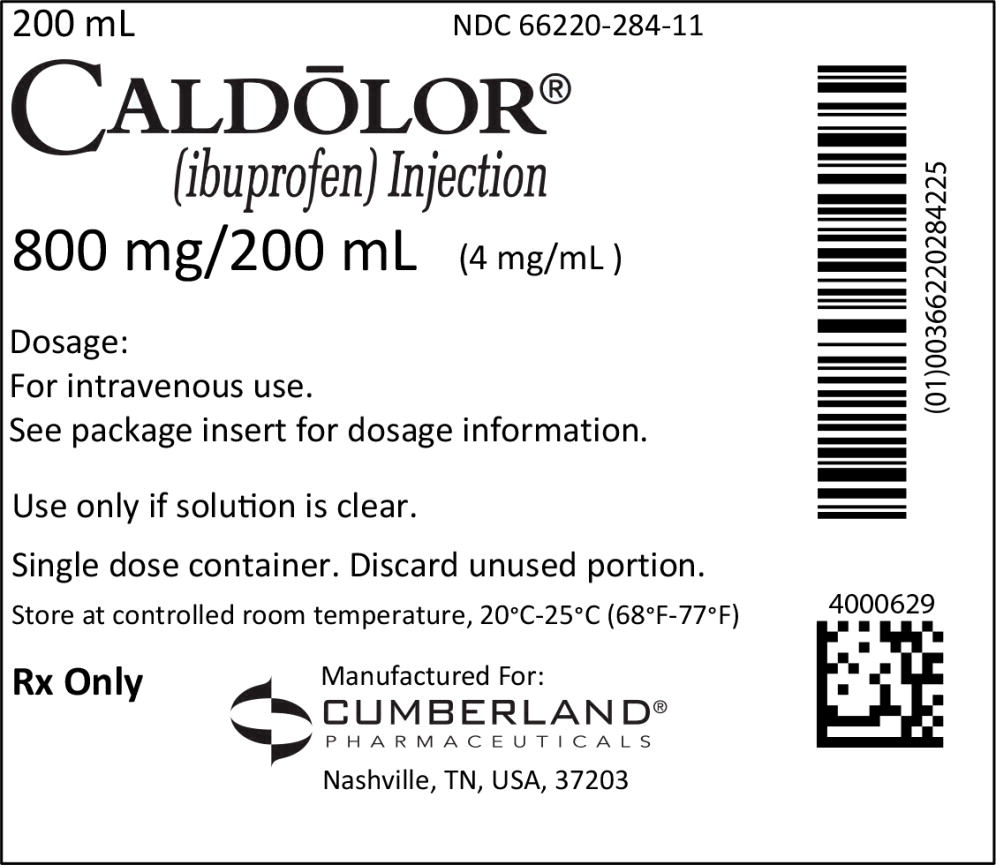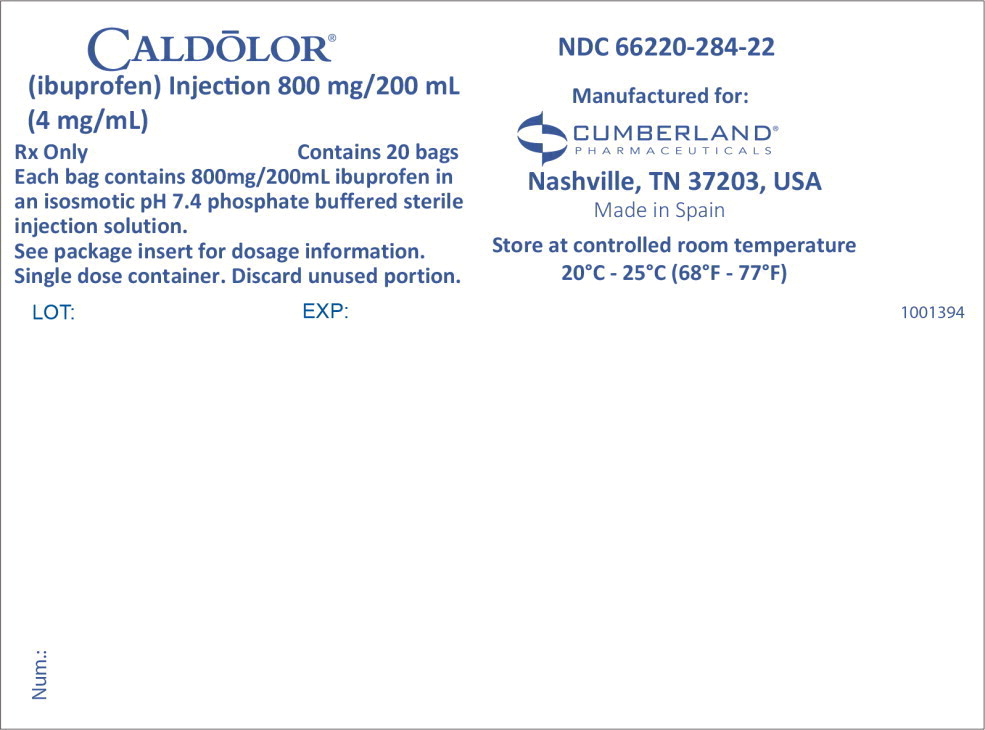 DRUG LABEL: Caldolor

NDC: 66220-287 | Form: INJECTION
Manufacturer: Cumberland Pharmaceuticals Inc.
Category: prescription | Type: HUMAN PRESCRIPTION DRUG LABEL
Date: 20250214

ACTIVE INGREDIENTS: ibuprofen
 800 mg/8 mL
INACTIVE INGREDIENTS: water; arginine; hydrochloric acid; nitrogen

HIGHLIGHTS OF PRESCRIBING INFORMATION

These highlights do not include all the information needed to use CALDOLOR® safely and effectively. See full prescribing information for CALDOLOR.
CALDOLOR (ibuprofen injection), for intravenous use
Initial U.S. Approval: 1974

RECENT MAJOR CHANGES

Warnings and Precautions (5.9) | 11/2024

WARNING: RISK OF SERIOUS CARDIOVASCULAR AND GASTROINTESTINAL EVENTS

See full prescribing information for complete boxed warning

- Non-steroidal anti-inflammatory drugs (NSAIDs) cause an increased risk of serious cardiovascular thrombotic events, including myocardial infarction and stroke, which can be fatal. This risk may occur early in treatment and may increase with duration of use. (5.1)
- CALDOLOR is contraindicated in the setting of coronary artery bypass graft (CABG) surgery. (4, 5.1)
- NSAIDs cause an increased risk of serious gastrointestinal (GI) adverse events including bleeding, ulceration, and perforation of the stomach or intestines, which can be fatal. These events can occur at any time during use and without warning symptoms. Elderly patients and patients with a prior history of peptic ulcer disease and/or GI bleeding are at greater risk for serious GI events. (5.2)

1 INDICATIONS AND USAGE

CALDOLOR is a nonsteroidal anti-inflammatory drug indicated in adults and pediatric patients aged 3 months and older for the:

- Management of mild to moderate pain and the management of moderate to severe pain as an adjunct to opioid analgesics (1)
- Reduction of fever (1)

2 DOSAGE AND ADMINISTRATION

- Use the lowest effective dosage for shortest duration consistent with individual patient treatment goals. (2.1)
- CALDOLOR Injection vials must be diluted before administration. (2.1)
- CALDOLOR Injection bags are ready to use. (2.1)
- Adult Pain: 400 mg to 800 mg intravenously over 30 minutes every 6 hours as necessary. (2.2)
- Adult Fever: 400 mg intravenously over 30 minutes, followed by 400 mg every 4 to 6 hours or 100-200 mg every 4 hours as necessary. (2.2)
- Pediatric (pain and fever) ages 12 to 17 years of age: 400 mg intravenously over 10 minutes every 4 to 6 hours as necessary. (2.3)
- Pediatric (pain and fever) aged 6 months to less than 12 years of age: 10 mg/kg intravenously over 10 minutes up to a maximum single dose of 400 mg every 4 to 6 hours as necessary. (2.3)
- Pediatric (pain and fever) aged 3 months to less than 6 months: 10 mg/kg intravenously over 10 minutes up to a maximum single dose of 100 mg. (2.3)

3 DOSAGE FORMS AND STRENGTHS

Injection:

- 800 mg/8 mL (100 mg/mL) single dose vial (3)
- 800 mg/200 mL (4 mg/mL) single dose, ready-to-use, polypropylene flexible bag (3)

4 CONTRAINDICATIONS

- Known hypersensitivity to ibuprofen or any component of the drug product (4)
- History of asthma, urticaria, or allergic-type reactions after taking aspirin or other NSAIDs (4)
- In the setting of CABG surgery (4)

5 WARNINGS AND PRECAUTIONS

- Hepatotoxicity: Inform patients of warning signs and symptoms of hepatotoxicity. Discontinue if abnormal liver tests persist or worsen or if clinical signs and symptoms of liver disease develop. (5.3)
- Hypertension: Patients taking some antihypertensive medications may have impaired response to these therapies when taking NSAIDs. Monitor blood pressure. (5.4, 7)
- Heart Failure and Edema: Avoid use of CALDOLOR in patients with severe heart failure unless benefits are expected to outweigh risk of worsening heart failure. (5.5)
- Renal Toxicity: Monitor renal function in patients with renal or hepatic impairment, heart failure, dehydration, or hypovolemia. Avoid use of CALDOLOR in patients with advanced renal disease unless benefits are expected to outweigh risk of worsening renal function. (5.6)
- Anaphylactic Reactions: Seek emergency help if an anaphylactic reaction occurs. (5.7)
- Exacerbation of Asthma Related to Aspirin Sensitivity: CALDOLOR is contraindicate d in patients with aspirin-sensitive asthma. Monitor patients with preexisting asthma (without aspirin sensitivity). (5.8)
- Serious Skin Reactions: Discontinue CALDOLOR at first appearance of skin rash or other signs of hypersensitivity (5.9)
- Drug Reaction with Eosinophilia and Systemic Symptoms (DRESS): Discontinue and evaluate clinically. (5.10)
- Fetal Toxicity: Limit use of NSAIDs, including CALDOLOR, between about 20 to 30 weeks in pregnancy due to the risk of oligohydramnios/fetal renal dysfunction. Avoid use of NSAIDs in women at about 30 weeks gestation and later in pregnancy due to the risks of oligohydramnios/fetal renal dysfunction and premature closure of the fetal ductus arteriosus. (5.11, 8.1)
- Hematologic Toxicity: Monitor hemoglobin or hematocrit in patients with any signs or symptoms of anemia. (5.11, 7)

6 ADVERSE REACTIONS

The most common adverse reactions are nausea, flatulence, vomiting, headache, hemorrhage and dizziness (>5%).

The most common adverse reactions in pediatric patients are infusion site pain, vomiting, nausea, anemia and headache (≥2%). (6)

To report SUSPECTED ADVERSE REACTIONS, contact Cumberland Pharmaceuticals Inc. at 1-877-484-2700 or FDA at 1-800-FDA-1088 or www.fda.gov/medwatch.

7 DRUG INTERACTIONS

- Drugs that Interfere with Hemostasis (e.g. warfarin, aspirin, SSRIs/SNRIs): Monitor patients for bleeding who are concomitantly taking CALDOLOR with drugs that interfere with hemostasis. Concomitant use of CALDOLOR and analgesic doses of aspirin is not generally recommended. (7)
- ACE Inhibitors, Angiotensin Receptor Blockers (ARB), or Beta-Blockers: Concomitant use with CALDOLOR may diminish the antihypertensive effect of these drugs. Monitor blood pressure .(7)
- ACE Inhibitors and ARBs: Concomitant use with CALDOLOR in elderly, volume depleted, or those with renal impairment may result in deterioration of renal function. In such high risk patients, monitor for signs of worsening renal function. (7)
- Diuretics: NSAIDs can reduce natriuretic effect of furosemide and thiazide diuretics. Monitor patients to assure diuretic efficacy including antihypertensive effects. (7)
- Digoxin: Concomitant use with CALDOLOR can increase serum concentration and prolong half-life of digoxin. Monitor serum digoxin levels. (7)

8 USE IN SPECIFIC POPULATIONS

Infertility: NSAIDs are associated with reversible infertility. Consider withdrawal of CALDOLOR in women who have difficulties conceiving. (8.3)

FULL PRESCRIBING INFORMATION

WARNING: RISK OF SERIOUS CARDIOVASCULAR AND GASTROINTESTINAL EVENTS

Cardiovascular Thrombotic Events

- Non-steroidal anti-inflammatory drugs (NSAIDs) cause an increased risk of serious cardiovascular thrombotic events, including myocardial infarction and stroke, which can be fatal. This risk may occur early in treatment and may increase with duration of use. [see Warnings and Precautions (5.1)].
- CALDOLOR is contraindicated in the setting of coronary artery bypass graft (CABG) surgery [see Contraindications (4) and Warnings and Precautions (5.1)].

Gastrointestinal Bleeding, Ulceration and Perforation

- NSAIDs cause an increased risk of serious gastrointestinal (GI) adverse events including bleeding, ulceration, and perforation of the stomach or intestines, which can be fatal. These events can occur at any time during use and without warning symptoms. Elderly patients and patients with a prior history of peptic ulcer disease and/or GI bleeding are at greater risk for serious GI events [see Warnings and Precautions (5.2)].

1 INDICATIONS AND USAGE

CALDOLOR is indicated in adults and pediatric patients aged 3 months and older for the:

- management of mild to moderate pain and the management of moderate to severe pain as an adjunct to opioid analgesics
- reduction of fever

2 DOSAGE AND ADMINISTRATION

2.1 Important Dosage and Administration Instructions

Use the lowest effective dosage for the shortest duration consistent with individual patient treatment goals [see Warnings and Precautions (5)].

After observing the response to initial therapy with CALDOLOR, the dose and frequency should be adjusted to suit an individual patient's needs. Do not exceed 3200 mg total daily dose in adults. Do not exceed 40 mg/kg or 2,400 mg, whichever is less, total daily dose in pediatric patients 6 months to 17 years of age.

The dosage is limited to a single dose not to exceed 10 mg/kg or 100 mg, whichever is less, in pediatric patients 3 months to less than 6 months of age.

To reduce the risk of renal adverse reactions, patients must be well hydrated prior to administration of CALDOLOR.

CALDOLOR injection 800 mg/8 mL (100 mg/mL) vials MUST BE DILUTED prior to administration.

Dilute to a final concentration of 4 mg/mL or less. Appropriate diluents include 0.9% Sodium Chloride Injection USP (normal saline), 5% Dextrose Injection USP (D5W), or Lactated Ringers Solution.

- 100 mg dose: Dilute 1 mL of CALDOLOR in at least 100 mL of diluent
- 200 mg dose: Dilute 2 mL of CALDOLOR in at least 100 mL of diluent
- 400 mg dose: Dilute 4 mL of CALDOLOR in at least 100 mL of diluent
- 800 mg dose: Dilute 8 mL of CALDOLOR in at least 200 mL of diluent

CALDOLOR injection 800 mg/200 mL (4 mg/mL) polypropylene flexible bags are ready to use, intended for 800 mg doses only.

For weight-based dosing at 10 mg/kg ensure that the concentration of CALDOLOR is 4 mg/mL or less.

Visually inspect parenteral drug products for particulate matter and discoloration prior to administration, whenever solution and container permit. If visibly opaque particles, discoloration or other foreign particulates are observed, the solution should not be used.

Diluted solutions are stable for up to 24 hours at ambient temperature (approximately 20° C to 25° C) and room lighting.

2.2 Adults

For Analgesia (pain):

The dose is 400 mg to 800 mg intravenously every 6 hours as necessary. Infusion time must be at least 30 minutes. Maximum daily dose is 3,200 mg.

For Fever:

The dose is 400 mg intravenously, followed by 400 mg every 4 to 6 hours or 100 mg to 200 mg every 4 hours as necessary. Infusion time must be at least 30 minutes. Maximum daily dose is 3,200 mg.

2.3 Pediatric Patients

For Analgesia (pain) and Fever:

Ages 12 to 17 years

The dose is 400 mg intravenously every 4 to 6 hours as necessary. Infusion time must be at least 10 minutes. Maximum daily dose is 40 mg/kg or 2,400 mg, whichever is less.

Ages 6 months to less than 12 years

The dose is 10 mg/kg intravenously up to a maximum single dose of 400 mg every 4 to 6 hours as necessary. Infusion time must be at least 10 minutes. Maximum daily dose is 40 mg/kg or 2,400 mg, whichever is less.

Pediatric Dosing as Necessary for Fever and Pain
Age Group | Dose | Dosing Interval | Min infusion time | Max daily dose
6 months to less than 12 years | 10 mg/kg up to 400 mg max | Every 4 to 6 hours as necessary | 10 minutes | *40 mg/kg or 2,400 mg
12 to 17 years | 400 mg | Every 4 to 6 hours as necessary | 10 minutes | *40 mg/kg or 2,400 mg
* Maximum daily dose is 40 mg/kg or 2,400 mg, whichever is less.

Ages 3 months to less than 6 months

The dose is a single dose at 10 mg/kg intravenously up to a maximum single dose of 100 mg. Infusion time must be at least 10 minutes.

3 DOSAGE FORMS AND STRENGTHS

CALDOLOR (ibuprofen injection) is a clear, colorless, non-pyrogenic, aqueous solution intended for intravenous use available in following strengths:

- 800 mg/8 mL (100 mg/mL) single dose vial
- 800 mg/200 mL (4 mg/mL) single dose, ready-to-use, polypropylene, flexible bag

4 CONTRAINDICATIONS

CALDOLOR is contraindicated in the following patients:

- Known hypersensitivity (e.g., anaphylactic reactions and serious skin reactions) to ibuprofen or any components of the drug product [see Warnings and Precautions (5.7, 5.9)]
- History of asthma, urticaria, or other allergic-type reactions after taking aspirin or other NSAIDs. Severe, sometimes fatal, anaphylactic reactions to NSAIDs have been reported in such patients [see Warnings and Precautions (5.7, 5.8)]
- In the setting of coronary artery bypass graft (CABG) surgery [see Warnings and Precautions (5.1)]

5 WARNINGS AND PRECAUTIONS

5.1 Cardiovascular Thrombotic Events

Clinical trials of several COX-2 selective and nonselective NSAIDs of up to three years duration have shown an increased risk of serious cardiovascular (CV) thrombotic events, including myocardial infarction (MI) and stroke, which can be fatal. Based on available data, it is unclear that the risk for CV thrombotic events is similar for all NSAIDs. The relative increase in serious CV thrombotic events over baseline conferred by NSAID use appears to be similar in those with and without known CV disease or risk factors for CV disease. However, patients with known CV disease or risk factors had a higher absolute incidence of excess serious CV thrombotic events, due to their increased baseline rate. Some observational studies found that this increased risk of serious CV thrombotic events began as early as the first weeks of treatment. The increase in CV thrombotic risk has been observed most consistently at higher doses.

To minimize the potential risk for an adverse CV event in NSAID-treated patients, use the lowest effective dose for the shortest duration possible. Physicians and patients should remain alert for the development of such events, throughout the entire treatment course, even in the absence of previous CV symptoms. Patients should be informed about the symptoms of serious CV events and the steps to take if they occur.

There is no consistent evidence that concurrent use of aspirin mitigates the increased risk of serious CV thrombotic events associated with NSAID use. The concurrent use of aspirin and an NSAID, such as ibuprofen, increases the risk of serious gastrointestinal (GI) events [see Warnings and Precautions (5.2)].

Status Post Coronary Artery Bypass Graft (CABG) Surgery

Two large, controlled clinical trials of a COX-2 selective NSAID for the treatment of pain in the first 10-14 days following CABG surgery found an increased incidence of myocardial infarction and stroke. NSAIDs are contraindicated in the setting of CABG [see Contraindications (4)].

Post-MI Patients

Observational studies conducted in the Danish National Registry have demonstrated that patients treated with NSAIDs in the post-MI period were at increased risk of reinfarction, CV-related death, and all-cause mortality beginning in the first week of treatment. In this same cohort, the incidence of death in the first year post-MI was 20 per 100 person years in NSAID-treated patients compared to 12 per 100 person years in non-NSAID exposed patients. Although the absolute rate of death declined somewhat after the first year post-MI, the increased relative risk of death in NSAID users persisted over at least the next four years of follow-up.

Avoid the use of CALDOLOR in patients with a recent MI unless the benefits are expected to outweigh the risk of recurrent CV thrombotic events. If CALDOLOR is used in patients with a recent MI, monitor patients for signs of cardiac ischemia.

5.2 Gastrointestinal Bleeding, Ulceration, and Perforation

NSAIDs, including ibuprofen, cause serious gastrointestinal (GI) adverse events including inflammation, bleeding, ulceration, and perforation of the esophagus, stomach, small intestine, or large intestine, which can be fatal. These serious adverse events can occur at any time, with or without warning symptoms, in patients treated with NSAIDs. Only one in five patients who develop a serious upper GI adverse event on NSAID therapy is symptomatic. Upper GI ulcers, gross bleeding, or perforation caused by NSAIDs occurred in approximately 1% of patients treated for 3-6 months and in about 2%-4% of patients treated for one year. However, even short-term therapy is not without risk.

Risk Factors for GI Bleeding, Ulceration and Perforation

Patients with a prior history of peptic ulcer disease and/or GI bleeding who used NSAIDs had a greater than 10-fold increased risk for developing a GI bleed compared to patients without these risk factors. Other factors that increase the risk of GI bleeding in patients treated with NSAIDs include longer duration of NSAID therapy; concomitant use of oral corticosteroids, aspirin, anticoagulants, or selective serotonin reuptake inhibitors (SSRIs); smoking; use of alcohol; older age; and poor general health status. Most postmarketing reports of fatal GI events occurred in elderly or debilitated patients. Additionally, patients with advanced liver disease and/or coagulopathy are at increased risk for GI bleeding.

Strategies to Minimize the GI Risks in NSAID-treated patients:

- Use the lowest effective dosage for the shortest possible duration.
- Avoid administration of more than one NSAID at a time.
- Avoid use in patients at higher risk unless benefits are expected to outweigh the increased risk of bleeding. For such patients, as well as those with active GI bleeding, consider alternate therapies other than NSAIDs.
- Remain alert for signs and symptoms of GI ulceration and bleeding during NSAID therapy.
- If a serious GI adverse event is suspected, promptly initiate evaluation and treatment, and discontinue CALDOLOR until a serious GI adverse event is ruled out.
- In the setting of concomitant use of low-dose aspirin for cardiac prophylaxis, monitor patients more closely for evidence of GI bleeding [see Drug Interactions (7)].

5.3 Hepatotoxicity

Elevations of ALT or AST (three or more times the upper limit of normal [ULN]) have been reported in approximately 1% of NSAID-treated patients in clinical trials. In addition, rare, sometimes fatal, cases of severe hepatic injury, including fulminant hepatitis, liver necrosis, and hepatic failure have been reported.

Elevations of ALT or AST (less than three times ULN) may occur in up to 15% of patients treated with NSAIDs, including ibuprofen.

Inform patients of the warning signs and symptoms of hepatotoxicity (e.g., nausea, fatigue, lethargy, diarrhea, pruritus, jaundice, right upper quadrant tenderness, and "flu-like" symptoms). If clinical signs and symptoms consistent with liver disease develop, or if systemic manifestations occur (e.g., eosinophilia, rash, etc.), discontinue CALDOLOR immediately, and perform a clinical evaluation of the patient.

5.4 Hypertension

NSAIDs, including CALDOLOR, can lead to new onset of hypertension or worsening of preexisting hypertension, either of which may contribute to the increased incidence of CV events. Patients taking angiotensin converting enzyme (ACE) inhibitors, thiazide diuretics, or loop diuretics may have impaired response to these therapies when taking NSAIDs [see Drug Interactions (7)].

Monitor blood pressure (BP) during the initiation of NSAID treatment and throughout the course of therapy.

5.5 Heart Failure and Edema

The Coxib and traditional NSAID Trialists' Collaboration meta-analysis of randomized controlled trials demonstrated an approximately two-fold increase in hospitalizations for heart failure in COX-2 selective-treated patients and nonselective NSAID-treated patients compared to placebo-treated patients. In a Danish National Registry study of patients with heart failure, NSAID use increased the risk of MI, hospitalization for heart failure, and death.

Additionally, fluid retention and edema have been observed in some patients treated with NSAIDs. Use of ibuprofen may blunt the CV effects of several therapeutic agents used to treat these medical conditions (e.g., diuretics, ACE inhibitors, or angiotensin receptor blockers [ARBs]) [see Drug Interactions (7)].

Avoid the use of CALDOLOR in patients with severe heart failure unless the benefits are expected to outweigh the risk of worsening heart failure. If CALDOLOR is used in patients with severe heart failure, monitor patients for signs of worsening heart failure.

5.6 Renal Toxicity and Hyperkalemia

Renal Toxicity

Long-term administration of NSAIDs has resulted in renal papillary necrosis and other renal injury.

Renal toxicity has also been seen in patients in whom renal prostaglandins have a compensatory role in the maintenance of renal perfusion. In these patients, administration of an NSAID may cause a dose dependent reduction in prostaglandin formation and, secondarily, in renal blood flow, which may precipitate overt renal decompensation. Patients at greatest risk of this reaction are those with impaired renal function, dehydration, hypovolemia, heart failure, liver dysfunction, those taking diuretics and ACE inhibitors or ARBs, and the elderly. Discontinuation of NSAID therapy is usually followed by recovery to the pretreatment state.

No information is available from controlled clinical studies regarding the use of CALDOLOR in patients with advanced renal disease. The renal effects of CALDOLOR may hasten the progression of renal dysfunction in patients with preexisting renal disease.

Correct volume status in dehydrated or hypovolemic patients prior to initiating CALDOLOR. Monitor renal function in patients with renal or hepatic impairment, heart failure, dehydration, or hypovolemia during use of CALDOLOR [see Drug Interactions (7)]. Avoid the use of CALDOLOR in patients with advanced renal disease unless the benefits are expected to outweigh the risk of worsening renal function. If CALDOLOR is used in patients with advanced renal disease, monitor patients for signs of worsening renal function.

Hyperkalemia

Increases in serum potassium concentration, including hyperkalemia, have been reported with use of NSAIDs, even in some patients without renal impairment. In patients with normal renal function, these effects have been attributed to a hyporeninemic-hypoaldosteronism state.

5.7 Anaphylactic Reactions

Ibuprofen has been associated with anaphylactic reactions in patients with and without known hypersensitivity to ibuprofen and in patients with aspirin-sensitive asthma [see Contraindications (4) and Warnings and Precautions (5.8)].

Seek emergency help if anaphylactic reaction occurs.

5.8 Exacerbation of Asthma Related to Aspirin Sensitivity

A subpopulation of patients with asthma may have aspirin-sensitive asthma which may include chronic rhinosinusitis complicated by nasal polyps; severe, potentially fatal bronchospasm; and/or intolerance to aspirin and other NSAIDs. Because cross-reactivity between aspirin and other NSAIDs has been reported in such aspirin-sensitive patients, CALDOLOR is contraindicated in patients with this form of aspirin sensitivity [see Contraindications (4)]. When CALDOLOR is used in patients with preexisting asthma (without known aspirin sensitivity), monitor patients for changes in the signs and symptoms of asthma.

5.9 Serious Skin Reactions

NSAIDs, including ibuprofen, can cause serious skin adverse reactions such as exfoliative dermatitis, Stevens-Johnson Syndrome (SJS), and toxic epidermal necrolysis (TEN), which can be fatal. NSAIDs can also cause fixed drug eruption (FDE). FDE may present as a more severe variant known as generalized bullous fixed drug eruption (GBFDE), which can be life-threatening. These serious events may occur without warning. Inform patients about the signs and symptoms of serious skin reactions, and to discontinue the use of CALDOLOR at the first appearance of skin rash or any other sign of hypersensitivity. CALDOLOR is contraindicated in patients with previous serious skin reactions to NSAIDs [see Contraindications (4)].

5.10 Drug Reaction with Eosinophilia and Systemic Symptoms (DRESS)

Drug Reaction with Eosinophilia and Systemic Symptoms (DRESS) has been reported in patients taking NSAIDs such as CALDOLOR. Some of these events have been fatal or life-threatening. DRESS typically, although not exclusively, presents with fever, rash, lymphadenopathy, and/or facial swelling. Other clinical manifestations may include hepatitis, nephritis, hematological abnormalities, myocarditis, or myositis. Sometimes symptoms of DRESS may resemble an acute viral infection. Eosinophilia is often present. Because this disorder is variable in its presentation, other organ systems not noted here may be involved. It is important to note that early manifestations of hypersensitivity, such as fever or lymphadenopathy, may be present even though rash is not evident. If such signs or symptoms are present, discontinue CALDOLOR and evaluate the patient immediately.

5.11 Fetal Toxicity

Premature Closure of Fetal Ductus Arteriosus

Avoid use of NSAIDs, including CALDOLOR, in pregnant women at about 30 weeks gestation and later. NSAIDs, including CALDOLOR, increase the risk of premature closure of the fetal ductus arteriosus at approximately this gestational age.

Oligohydramnios/Neonatal Renal Impairment

Use of NSAIDs, including CALDOLOR, at about 20 weeks gestation or later in pregnancy may cause fetal renal dysfunction leading to oligohydramnios and, in some cases, neonatal renal impairment. These adverse outcomes are seen, on average, after days to weeks of treatment, although oligohydramnios has been infrequently reported as soon as 48 hours after NSAID initiation.

Oligohydramnios is often, but not always, reversible with treatment discontinuation. Complications of prolonged oligohydramnios may, for example, include limb contractures and delayed lung maturation. In some postmarketing cases of impaired neonatal renal function, invasive procedures such as exchange transfusion or dialysis were required.

If NSAID treatment is necessary between about 20 weeks and 30 weeks gestation, limit CALDOLOR use to the lowest effective dose and shortest duration possible. Consider ultrasound monitoring of amniotic fluid if CALDOLOR treatment extends beyond 48 hours. Discontinue CALDOLOR if oligohydramnios occurs and follow up according to clinical practice [see Use in Specific Populations (8.1)].

5.12 Hematologic Toxicity

Anemia has occurred in NSAID-treated patients. This may be due to occult or gross GI blood loss, fluid retention, or an incompletely described effect on erythropoiesis. If a patient treated with CALDOLOR has any signs or symptoms of anemia, monitor hemoglobin or hematocrit.

NSAIDs, including CALDOLOR may increase the risk of bleeding events. Co-morbid conditions such as coagulation disorder, concomitant use of warfarin, other anticoagulants, antiplatelet agents (e.g., aspirin), serotonin reuptake inhibitors (SSRIs) and serotonin norepinephrine reuptake inhibitors (SNRIs) may increase this risk. Monitor these patients for signs of bleeding [see Drug Interactions (7)].

CALDOLOR must be diluted prior to use. Infusion of the drug product without dilution can cause hemolysis [see Dosage and Administration (2.1)].

5.13 Masking of Inflammation and Fever

The pharmacological activity of CALDOLOR in reducing inflammation, and possibly fever, may diminish the utility of diagnostic signs in detecting infections.

5.14 Laboratory Monitoring

Because serious GI bleeding, hepatotoxicity, and renal injury can occur without warning symptoms or signs, consider monitoring patients on long-term NSAID treatment with a CBC and a chemistry profile periodically [see Warnings and Precautions (5.2, 5.3, 5.6)].

5.15 Ophthalmological Effects

Blurred or diminished vision, scotomata, and changes in color vision have been reported with oral ibuprofen. Discontinue ibuprofen if a patient develops such complaints and refer the patient for an ophthalmologic examination that includes central visual fields and color vision testing.

5.16 Aseptic Meningitis

Aseptic meningitis with fever and coma has been observed in patients on oral ibuprofen therapy. Although it is probably more likely to occur in patients with systemic lupus erythematosus and related connective tissue diseases, it has been reported in patients who do not have underlying chronic disease. If signs or symptoms of meningitis develop in a patient on ibuprofen, give consideration to whether or not the signs or symptoms are related to ibuprofen therapy.

6 ADVERSE REACTIONS

The following serious adverse reactions are discussed in greater detail in other sections of the labeling:

- Cardiovascular Thrombotic Events [see Warnings and Precautions (5.1)]
- GI Bleeding, Ulceration and Perforation [see Warnings and Precautions (5.2)]
- Hepatotoxicity [see Warnings and Precautions (5.3)]
- Hypertension [see Warnings and Precautions (5.4)]
- Heart Failure and Edema [see Warnings and Precautions (5.5)]
- Renal Toxicity and Hyperkalemia [see Warnings and Precautions (5.6)]
- Anaphylactic reactions [see Warnings and Precautions (5.7)]
- Serious Skin Reactions [see Warnings and Precautions (5.9)]
- Hematologic Toxicity [see Warnings and Precautions (5.11)]

6.1 Clinical Trials Experience

Because clinical trials are conducted under widely varying conditions, adverse reaction rates observed in the clinical trials of a drug cannot be compared directly to rates in the clinical trials of another drug and may not reflect the rates observed in practice.

Adult Population

During clinical development, 560 patients were exposed to CALDOLOR, 438 in pain and 122 with fever. In the pain studies, CALDOLOR was started intra-operatively and administered at a dose of 400 mg or 800 mg every six hours for up to three days. In the fever studies, CALDOLOR was administered at doses of 100 mg, 200 mg, or 400 mg every four or six hours for up to 3 days. The most frequent type of adverse reaction occurring with oral ibuprofen is gastrointestinal.

Pain Studies

The incidence rates of adverse reactions listed in the following table were derived from multi-center, controlled clinical studies in post-operative patients comparing CALDOLOR to placebo in patients also receiving morphine as needed for post-operative pain.

Table 1: Post-operative Patients with Adverse Reactions Observed in ≥ 3% of Patients in any CALDOLOR Treatment Group in Pain Studies*
Event | CALDOLOR |  | Placebo (N=287)
Event | 400 mg (N=134) | 800 mg (N=304) | Placebo (N=287)
Any Reaction | 118 (88%) | 260 (86%) | 258 (90%)
Nausea | 77 (57%) | 161 (53%) | 179 (62%)
Vomiting | 30 (22%) | 46 (15%) | 50 (17%)
Flatulence | 10 (7%) | 49 (16%) | 44 (15%)
Headache | 12 (9%) | 35 (12%) | 31 (11%)
Hemorrhage | 13 (10%) | 13 (4%) | 16 (6%)
Dizziness | 8 (6%) | 13 (4%) | 5 (2%)
Edema peripheral | 1 (<1%) | 9 (3%) | 4 (1%)
Urinary retention | 7 (5%) | 10 (3%) | 10 (3%)
Anemia | 5 (4%) | 7 (2%) | 6 (2%)
Decreased hemoglobin | 4 (3%) | 6 (2%) | 3 (1%)
Dyspepsia | 6 (4%) | 4 (1%) | 2 (<1%)
Wound hemorrhage | 4 (3%) | 4 (1%) | 4 (1%)
Abdominal discomfort | 4 (3%) | 2 (<1%) | 0
Cough | 4 (3%) | 2 (<1%) | 1 (<1%)
Hypokalemia | 5 (4%) | 3 (<1%) | 8 (3%)
* All patients received concomitant morphine during these studies.

Fever Studies

Fever studies were conducted in febrile hospitalized patients with malaria and febrile hospitalized patients with varying causes of fever. In hospitalized febrile patients with malaria, the adverse reactions observed in at least two CALDOLOR-treated patients included abdominal pain and nasal congestion.

In hospitalized febrile patients (all causes), adverse reactions observed in more than two patients in any given treatment group are presented in the table below.

Table 2: Patients with Adverse Reactions Observed in ≥ 3% of Patients in any CALDOLOR Treatment Group in All-Cause Fever Study
Event | CALDOLOR |  |  | Placebo N=28
Event | 100 mg N=30 | 200 mg N=30 | 400 mg N=31 | Placebo N=28
Any Reaction | 27 (87%) | 25 (83%) | 23 (74%) | 25 (89%)
Anemia | 5 (17%) | 6 (20%) | 11 (36%) | 4 (14%)
Eosinophilia | 7 (23%) | 7 (23%) | 8 (26%) | 7 (25%)
Hypokalemia | 4 (13%) | 4 (13%) | 6 (19%) | 5 (18%)
Hypoproteinemia | 3 (10%) | 0 | 4 (13%) | 2 (7%)
Neutropenia | 2 (7%) | 2 (7%) | 4 (13%) | 2 (7%)
Blood urea increased | 0 | 0 | 3 (10%) | 0
Hypernatremia | 2 (7%) | 0 | 3 (10%) | 0
Hypertension | 0 | 0 | 3 (10%) | 0
Hypoalbuminemia | 3 (10%) | 1 (3%) | 3 (10%) | 1 (4%)
Hypotension | 0 | 2 (7%) | 3 (10%) | 1 (4%)
Diarrhea | 3 (10%) | 3 (10%) | 2 (7%) | 2 (7%)
Pneumonia bacterial | 3 (10%) | 1 (3%) | 2 (7%) | 0
Blood LDH increased | 3 (10%) | 2 (7%) | 1 (3%) | 1 (4%)
Thrombocythemia | 3 (10%) | 2 (7%) | 1 (3%) | 0
Bacteremia | 4 (13%) | 0 | 0 | 0

Pediatric Population

A total of 143 pediatric patients ages 6 months and older have received CALDOLOR in controlled clinical trials. The most common adverse reactions (incidence greater than or equal to 2%) in pediatric patients treated with CALDOLOR were infusion site pain, vomiting, nausea, anemia and headache.

Twenty-one hospitalized patients ages 3 months to less than 6 months were treated with CALDOLOR for pain or fever in an open-label, non-controlled clinical study; 18 of 21 patients were treated with a single dose.

6.2 Postmarketing Experience

The following adverse reactions have been identified during postapproval use of ibuprofen. Because these reactions are reported voluntarily from a population of uncertain size, it is not always possible to reliably estimate their frequency or establish a causal relationship to drug exposure.

Skin and Appendages: Exfoliative dermatitis, Stevens-Johnson Syndrome (SJS), toxic epidermal necrolysis (TEN), and fixed drug eruption (FDE).

7 DRUG INTERACTIONS

See Table 3 for clinically significant drug interactions with ibuprofen.

Table 3: Clinically Significant Drug Interactions with Ibuprofen
Drugs That Interfere with Hemostasis
Clinical Impact: | - Ibuprofen and anticoagulants such as warfarin have a synergistic effect on bleeding. The concomitant use of ibuprofen and anticoagulants have an increased risk of serious bleeding compared to the use of either drug alone. - Serotonin released by platelets plays an important role in hemostasis. Case-control and cohort epidemiological studies showed that concomitant use of drugs that interfere with serotonin reuptake and an NSAID may potentiate the risk of bleeding more than an NSAID alone.
Intervention: | Monitor patients with concomitant use of CALDOLOR with anticoagulants (e.g., warfarin), antiplatelet agents (e.g., aspirin), selective serotonin reuptake inhibitors (SSRIs), and serotonin norepinephrine reuptake inhibitors (SNRIs) for signs of bleeding [see Warnings and Precautions (5.11)].
Aspirin
Clinical Impact: | Pharmacodynamic (PD) studies have demonstrated interference with the antiplatelet activity of aspirin when ibuprofen 400 mg, given three times daily, is administered with enteric-coated low-dose aspirin. The interaction exists even following a once-daily regimen of ibuprofen 400 mg, particularly when ibuprofen is dosed prior to aspirin. The interaction is alleviated if immediate-release low-dose aspirin is dosed at least 2 hours prior to a once daily regimen of ibuprofen; however, this finding cannot be extended to enteric-coated low-dose aspirin [see Clinical Pharmacology (12.2)]. Controlled clinical studies showed that the concomitant use of NSAIDs and analgesic doses of aspirin does not produce any greater therapeutic effect than the use of NSAIDs alone. In a clinical study, the concomitant use of an NSAID and aspirin was associated with a significantly increased incidence of GI adverse reactions as compared to use of the NSAID alone [see Warnings and Precautions (5.2)].
Intervention: | Because there may be an increased risk of cardiovascular events due to the interference of ibuprofen with the antiplatelet effect of aspirin, for patients taking low-dose aspirin for cardioprotection who require analgesics, consider use of an NSAID that does not interfere with the antiplatelet effect of aspirin, or non-NSAID analgesics, where appropriate. Concomitant use of CALDOLOR and analgesic doses of aspirin is not generally recommended because of the increased risk of bleeding [see Warnings and Precautions (5.11)]. CALDOLOR is not a substitute for low dose aspirin for cardiovascular protection.
ACE Inhibitors, Angiotensin Receptor Blockers, and Beta-Blockers
Clinical Impact: | - NSAIDs may diminish the antihypertensive effect of angiotensin converting enzyme (ACE) inhibitors, angiotensin receptor blockers (ARBs), or beta-blockers (including propranolol). - In patients who are elderly, volume-depleted (including those on diuretic therapy), or have renal impairment, co-administration of an NSAID with ACE inhibitors or ARBs may result in deterioration of renal function, including possible acute renal failure. These effects are usually reversible.
Intervention: | - During concomitant use of CALDOLOR and ACE-inhibitors, ARBs, or beta- blockers, monitor blood pressure to ensure that the desired blood pressure is obtained. - During concomitant use of CALDOLOR and ACE-inhibitors or ARBs in patients who are elderly, volume-depleted, or have impaired renal function, monitor for signs of worsening renal function [see Warnings and Precautions (5.6)]. - When these drugs are administered concomitantly, patients should be adequately hydrated. Assess renal function at the beginning of the concomitant treatment and periodically thereafter.
Diuretics
Clinical Impact: | Clinical studies, as well as post-marketing observations, showed that NSAIDs reduced the natriuretic effect of loop diuretics (e.g., furosemide) and thiazide diuretics in some patients. This effect has been attributed to the NSAID inhibition of renal prostaglandin synthesis.
Intervention: | During concomitant use of CALDOLOR with diuretics, observe patients for signs of worsening renal function, in addition to assuring diuretic efficacy including antihypertensive effects [see Warnings and Precautions (5.6)].
Digoxin
Clinical Impact: | The concomitant use of ibuprofen with digoxin has been reported to increase the serum concentration and prolong the half-life of digoxin.
Intervention: | During concomitant use of CALDOLOR and digoxin, monitor serum digoxin levels.
Lithium
Clinical Impact: | NSAIDs have produced elevations in plasma lithium levels and reductions in renal lithium clearance. The mean minimum lithium concentration increased 15%, and the renal clearance decreased by approximately 20%. This effect has been attributed to NSAID inhibition of renal prostaglandin synthesis.
Intervention: | During concomitant use of CALDOLOR and lithium, monitor patients for signs of lithium toxicity.
Methotrexate
Clinical Impact: | Concomitant use of NSAIDs and methotrexate may increase the risk for methotrexate toxicity (e.g., neutropenia, thrombocytopenia, renal dysfunction).
Intervention: | During concomitant use of CALDOLOR and methotrexate, monitor patients for methotrexate toxicity.
Cyclosporine
Clinical Impact: | Concomitant use of CALDOLOR and cyclosporine may increase cyclosporine's nephrotoxicity.
Intervention: | During concomitant use of CALDOLOR and cyclosporine, monitor patients for signs of worsening renal function.
NSAIDs and Salicylates
Clinical Impact: | Concomitant use of ibuprofen with other NSAIDs or salicylates (e.g., diflunisal, salsalate) increases the risk of GI toxicity, with little or no increase in efficacy [see Warnings and Precautions (5.2)].
Intervention: | The concomitant use of ibuprofen with other NSAIDs or salicylates is not recommended.
Pemetrexed
Clinical Impact: | Concomitant use of CALDOLOR and pemetrexed, may increase the risk of pemetrexed-associated myelosuppression, renal, and GI toxicity (see the pemetrexed prescribing information).
Intervention: | - During concomitant use of CALDOLOR and pemetrexed, in patients with renal impairment whose creatinine clearance ranges from 45 to 79 mL/min, monitor for myelosuppression, renal and GI toxicity. - NSAIDs with short elimination half-lives (e.g., diclofenac, indomethacin) should be avoided for a period of two days before, the day of, and two days following administration of pemetrexed. - In the absence of data regarding potential interaction between pemetrexed and NSAIDs with longer half-lives (e.g., meloxicam, nabumetone), patients taking these NSAIDs should interrupt dosing for at least five days before, the day of, and two days following pemetrexed administration.

8 USE IN SPECIFIC POPULATIONS

8.1 Pregnancy

Risk Summary

Use of NSAIDs, including CALDOLOR, can cause premature closure of the fetal ductus arteriosus and fetal renal dysfunction leading to oligohydramnios and, in some cases, neonatal renal impairment. Because of these risks, limit dose and duration of CALDOLOR use between about 20 and 30 weeks of gestation, and avoid CALDOLOR use at about 30 weeks of gestation and later in pregnancy (see Clinical Considerations, Data).

Premature Closure of Fetal Ductus Arteriosus

Use of NSAIDs, including CALDOLOR, at about 30 weeks gestation or later in pregnancy increases the risk of premature closure of the fetal ductus arteriosus.

Oligohydramnios/Neonatal Renal Impairment

Use of NSAIDs at about 20 weeks gestation or later in pregnancy has been associated with cases of fetal renal dysfunction leading to oligohydramnios, and in some cases, neonatal renal impairment.

Data from observational studies regarding other potential embryofetal risks of NSAID use in women in the first or second trimesters of pregnancy are inconclusive.

Based on animal data, prostaglandins have been shown to have an important role in endometrial vascular permeability, blastocyst implantation, and decidualization. In animal studies, administration of prostaglandin synthesis inhibitors such as ibuprofen resulted in increased pre- and post-implantation loss. Prostaglandins also have been shown to have an important role in fetal kidney development. In published animal studies, prostaglandin synthesis inhibitors have been reported to impair kidney development when administered at clinically relevant doses.

The estimated background risk of major birth defects and miscarriage for the indicated population(s) is unknown. All pregnancies have a background risk of birth defect, loss, or other adverse outcomes. In the U.S. general population, the estimated background risk of major birth defects and miscarriage in clinically recognized pregnancies is 2% to 4% and 15% to 20%, respectively.

Clinical Considerations

Fetal/Neonatal Adverse Reactions

Premature Closure of Fetal Ductus Arteriosus:

Avoid use of NSAIDs in women at about 30 weeks gestation and later in pregnancy, because NSAIDs, including CALDOLOR, can cause premature closure of the fetal ductus arteriosus (see Data).

Oligohydramnios/Neonatal Renal Impairment:

If an NSAID is necessary at about 20 weeks gestation or later in pregnancy, limit the use to the lowest effective dose and shortest duration possible. If CALDOLOR treatment extends beyond 48 hours, consider monitoring with ultrasound for oligohydramnios. If oligohydramnios occurs, discontinue CALDOLOR and follow up according to clinical practice (see Data).

Labor or Delivery

There are no studies on the effects of CALDOLOR during labor or delivery. In animal studies, NSAIDs, including ibuprofen, inhibit prostaglandin synthesis, cause delayed parturition, and increase the incidence of stillbirth.

Data

Human Data

Premature Closure of Fetal Ductus Arteriosus:

Published literature reports that the use of NSAIDs at about 30 weeks of gestation and later in pregnancy may cause premature closure of the fetal ductus arteriosus.

Oligohydramnios/Neonatal Renal Impairment:

Published studies and postmarketing reports describe maternal NSAID use at about 20 weeks gestation or later in pregnancy associated with fetal renal dysfunction leading to oligohydramnios, and in some cases, neonatal renal impairment. These adverse outcomes are seen, on average, after days to weeks of treatment, although oligohydramnios has been infrequently reported as soon as 48 hours after NSAID initiation. In many cases, but not all, the decrease in amniotic fluid was transient and reversible with cessation of the drug. There have been a limited number of case reports of maternal NSAID use and neonatal renal dysfunction without oligohydramnios, some of which were irreversible. Some cases of neonatal renal dysfunction required treatment with invasive procedures, such as exchange transfusion or dialysis.

Methodological limitations of these postmarketing studies and reports include lack of a control group; limited information regarding dose, duration, and timing of drug exposure; and concomitant use of other medications. These limitations preclude establishing a reliable estimate of the risk of adverse fetal and neonatal outcomes with maternal NSAID use. Because the published safety data on neonatal outcomes involved mostly preterm infants, the generalizability of certain reported risks to the full-term infant exposed to NSAIDs through maternal use is uncertain.

Animal Data

In a published study, female rabbits given 7.5, 20, or 60 mg/kg ibuprofen (0.04, 0.12, or 0.36-times the maximum recommended human daily dose of 3200 mg of ibuprofen based on body surface area) from Gestation Days 1 to 29, no clear treatment-related adverse developmental effects were noted. This dose was associated with significant maternal toxicity (stomach ulcers, gastric lesions). In the same publication, female rats were administered 7.5, 20, 60, 180 mg/kg ibuprofen (0.02, 0.06, 0.18, 0.54-times the maximum daily dose) did not result in clear adverse developmental effects. Maternal toxicity (gastrointestinal lesions) was noted at 20 mg/kg and above.

In a published study, rats were orally dosed with 300 mg/kg ibuprofen (0.912-times the maximum human daily dose of 3200 mg based on body surface area) during Gestation Days 9 and 10 (critical time points for heart development in rats). Ibuprofen treatment resulted in an increase in the incidence of membranous ventricular septal defects. This dose was associated with significant maternal toxicity including gastrointestinal toxicity. One incidence each of a membranous ventricular septal defect and gastroschisis was noted in fetuses from rabbits treated with 500 mg/kg (3-times the maximum human daily dose) from Gestation Day 9-11.

8.2 Lactation

Risk Summary

No lactation studies have been conducted with CALDOLOR; however, limited published literature reports that, following oral administration, ibuprofen is present in human milk at relative infant doses of 0.06% to 0.6% of the maternal weight-adjusted daily dose. There are no reports of adverse effects on the breastfed infant and no effects on milk production. The developmental and health benefits of breastfeeding should be considered along with the mother's clinical need for CALDOLOR and any potential adverse effects on the breastfed infant from the CALDOLOR or from the underlying maternal condition.

8.3 Females and Males of Reproductive Potential

Infertility

Females

Based on the mechanism of action, the use of prostaglandin-mediated NSAIDs, including CALDOLOR, may delay or prevent rupture of ovarian follicles, which has been associated with reversible infertility in some women. Published animal studies have shown that administration of prostaglandin synthesis inhibitors has the potential to disrupt prostaglandin- mediated follicular rupture required for ovulation. Small studies in women treated with NSAIDs have also shown a reversible delay in ovulation. Consider withdrawal of NSAIDs, including CALDOLOR in women who have difficulties conceiving or who are undergoing investigation of infertility.

8.4 Pediatric Use

The safety and effectiveness of CALDOLOR have been established for the treatment of pain and fever in pediatric patients aged 3 months and older. Use of CALDOLOR for these indications is supported by evidence from one open-label and acetaminophen controlled study of fever and additional safety data from four studies in 164 pediatric patients, supportive pediatric data from other approved ibuprofen products, and evidence from adequate and well-controlled studies in adults [see Dosage and Administration (2), Adverse Reactions (6.1), Clinical Pharmacology (12.3), Clinical Studies (14)].

Safety and effectiveness of CALDOLOR in pediatric patients less than 3 months of age for treatment of pain and fever have not been established.

8.5 Geriatric Use

Elderly patients, compared to younger patients, are at greater risk for NSAID-associated serious cardiovascular, gastrointestinal, and/or renal adverse reactions. If the anticipated benefit for the elderly patient outweighs these potential risks, start dosing at the low end of the dosing range, and monitor patients for adverse effects [see Warnings and Precautions (5.1, 5.2, 5.3, 5.6, 5.13)].

Clinical studies of CALDOLOR did not include sufficient numbers of subjects aged 65 and over to determine whether they respond differently from younger subjects. Dose selection for an elderly patient should be cautious, usually starting at the low end of the dosing range, reflecting the greater frequency of decreased hepatic, renal, or cardiac function, and of concomitant disease or other drug therapy. Elderly patients are at increased risk for serious GI adverse events.

10 OVERDOSAGE

Symptoms following acute NSAID overdosages have been typically limited to lethargy, drowsiness, nausea, vomiting, and epigastric pain, which have been generally reversible with supportive care. Gastrointestinal bleeding has occurred. Hypertension, acute renal failure, respiratory depression, and coma have occurred, but were rare [see Warnings and Precautions (5.1, 5.2, 5.4, 5.6)].

Manage patients with symptomatic and supportive care following an NSAID overdosage. There are no specific antidotes. Forced diuresis, alkalinization of urine, hemodialysis, or hemoperfusion may not be useful due to high protein binding.

For additional information about overdosage treatment contact a poison control center at 1-800-222-1222.

11 DESCRIPTION

CALDOLOR (ibuprofen injection) is a nonsteroidal anti-inflammatory drug, available as an 800 mg/8 mL single dose vial (100 mg/mL) and 800 mg/200 mL (4 mg/mL) polypropylene, single dose, ready-to-use, flexible bag for intravenous administration. The chemical name is ibuprofen, which is (±)-2-(p-isobutylphenyl) propionic acid. Ibuprofen is a white powder with a melting point of 74°C to 77°C. It has a molecular weight of 206.28. It is very slightly soluble in water (<1 mg/mL) and readily soluble in organic solvents such as ethanol and acetone. The structural formula of ibuprofen is represented below:

CALDOLOR 800 mg/8 mL (100 mg/mL) vial: Each 1 mL of solution contains 100 mg of ibuprofen, USP, 78 mg of arginine (at a molar ratio of 0.92:1 arginine:ibuprofen), and 10% arginine solution and hydrochloric acid as pH adjusters in Water for Injection, USP. The solution pH is about 7.4.

CALDOLOR 800 mg/200 mL (4 mg/mL) polypropylene flexible bag: Each 1 mL of solution contains 4 mg of ibuprofen, USP, 3.11 mg of dibasic sodium phosphate, as a buffering agent; 6.30 mg sodium chloride as a tonicity agent; and sodium hydroxide as a pH adjuster in Water for Injection, USP. The solution is iso-osmotic with an approximate pH of 7.4.

CALDOLOR is sterile and is intended for intravenous administration only.

12 CLINICAL PHARMACOLOGY

12.1 Mechanism of Action

Ibuprofen has analgesic, anti-inflammatory, and antipyretic properties.

The mechanism of action of CALDOLOR, like that of other NSAIDs, is not completely understood but involves inhibition of cyclooxygenase (COX-1 and COX-2).

Ibuprofen is a potent inhibitor of prostaglandin synthesis in vitro. Ibuprofen concentrations reached during therapy have produced in vivo effects. Prostaglandins sensitize afferent nerves and potentiate the action of bradykinin in inducing pain in animal models. Prostaglandins are mediators of inflammation. Because ibuprofen is an inhibitor of prostaglandin synthesis, its mode of action may be due to a decrease of prostaglandins in peripheral tissues.

12.2 Pharmacodynamics

In a healthy volunteer study, ibuprofen 400 mg given once daily, administered 2 hours prior to immediate-release aspirin (81 mg) for 6 days, showed an interaction with the antiplatelet activity of aspirin as measured by % serum thromboxane B2 (TxB2) inhibition at 24 hours following the day-6 aspirin dose [53%]. An interaction was still observed, but minimized, when ibuprofen 400 mg given once-daily was administered as early as 8 hours prior to the immediate-release aspirin dose [90.7%]. However, there was no interaction with the antiplatelet activity of aspirin when ibuprofen 400 mg, given once daily, was administered 2 hours after (but not concomitantly, 15 min, or 30 min after) the immediate-release aspirin dose [99.2%].

In another study, where immediate-release aspirin 81 mg was administered once daily with ibuprofen 400 mg given three times daily (1, 7, and 13 hours post-aspirin dose) for 10 consecutive days, the mean % serum thromboxane B2 (TxB2) inhibition suggested no interaction with the antiplatelet activity of aspirin [98.3%]. However, there were individual subjects with serum TxB2 inhibition below 95%, with the lowest being 90.2%.

When a similarly designed study was conducted with enteric-coated aspirin, where healthy subjects were administered enteric-coated aspirin 81 mg once daily for 6 days and ibuprofen 400 mg three times daily (2, 7 and 12 h post-aspirin dose) for 6 days, there was an interaction with the antiplatelet activity at 24 hours following the day-6 aspirin dose [67%]. [See Drug Interactions (7)].

12.3 Pharmacokinetics

Ibuprofen is a racemic mixture of [-]R- and [+]S-isomers. In vivo and in vitro studies indicate that the [+]S-isomer is responsible for clinical activity. The [-]R-form, while thought to be pharmacologically inactive, is slowly and incompletely (~60%) interconverted into the active [+]S species in adults. The [-]R-isomer serves as a circulating reservoir to maintain levels of active drug. The pharmacokinetic parameters of CALDOLOR determined in a study with volunteers are presented below.

Table 4: Pharmacokinetic Parameters of Intravenous Ibuprofen
 | 400 mg* CALDOLOR Mean (SD) | 800 mg* CALDOLOR Mean (SD)
Number of Patients | 12 | 12
AUC (mcg·h/mL) | 109.3 (28.9) | 192.8 (35.7)
Cmax (mcg/mL) | 39.2 (6.09) | 72.6 (9.61)
KEL (1/h) | 0.32 (0.06) | 0.29 (0.04)
T1/2 (h) | 2.22 (0.45) | 2.44 (0.31)
AUC = Area-under-the-curve
Cmax = Peak plasma concentration
CV = Coefficient of Variation
KEL = First-order elimination rate constant
T1/2 = Elimination half-life
* = 60 minute infusion time

The pharmacokinetic parameters of CALDOLOR determined in a study with febrile pediatric patients are presented in Table 5. It was observed that the median Tmax was at the end of the infusion and that CALDOLOR had a shorter elimination half-life in pediatric patients compared to adults.

Table 5: Pharmacokinetic Parameters of 10 mg/kg Intravenous** Ibuprofen, Pediatric Patients, by Age Group
 | 3 months to <6 months^ Mean (SD) | 6 months to <2 years Mean (SD) | 2 years to <6 years Mean (SD) | 6 years to 16 years Mean (SD)
Number of Patients | 20 | 5 | 12 | 25
AUC (mcg·h/mL) | 69.63 (19.28) | 71.1 (26.4) | 79.2 (29.3) | 80.7 (29.8)
Cmax (mcg/mL) | 59.75 (12.85) | 59.2 (20.6) | 64.2 (22.1) | 61.9 (16.5)
Tmax (min)* | 10 | 10 (10-30) | 12 (10-46) | 10 (10-40)
T1/2 (h) | 1.3 | 1.8 (0.5) | 1.5 (0.6) | 1.55 (0.41)
*Median (minimum-maximum)
^Open-label study with hospitalized pediatric patients with pain or fever
**= 10 minute infusion time

Ibuprofen, like most NSAIDs, is highly protein bound (>99% bound at 20 mcg/mL). Protein binding is saturable, and at concentrations >20 mcg/mL binding is nonlinear. Based on oral dosing data, there is an age- or fever-related change in volume of distribution for ibuprofen.

Drug Interaction Studies

Aspirin: When NSAIDs were administered with aspirin, the protein binding of NSAIDs were reduced, although the clearance of free NSAID was not altered. The clinical significance of this interaction is not known. See Table 3 for clinically significant drug interactions of NSAIDs with aspirin [see Drug Interactions (7)].

13 NONCLINICAL TOXICOLOGY

13.1 Carcinogenesis, Mutagenesis, Impairment of Fertility

Carcinogenesis

Long-term studies in animals to evaluate the carcinogenic potential of ibuprofen have not been conducted.

Mutagenesis

In published studies, ibuprofen was not mutagenic in the in vitro bacterial reverse mutation assay (Ames assay).

Impairment of Fertility

In a published study, dietary administration of ibuprofen to male and female rats 8-weeks prior to and during mating at dose levels of 20 mg/kg (0.06-times the MRHD based on body surface area comparison) did not impact male or female fertility or litter size.

In other studies, adult mice were administered ibuprofen intraperitoneally at a dose of 5.6 mg/kg/day (0.0085-times the MRHD based on body surface area comparison) for 35 or 60 days in males and 35 days in females. There was no effect on sperm motility or viability in males, but decreased ovulation was reported in females.

14 CLINICAL STUDIES

14.1 Analgesia (Pain)

The effect of CALDOLOR on acute pain was evaluated in three multi-center, randomized, double-blind, placebo-controlled studies.

In a study of women who had undergone an elective abdominal hysterectomy, 319 patients were randomized and treated with CALDOLOR 800 mg or placebo administered every 6 hours (started intra-operatively) and morphine administered on an as-needed basis. Efficacy was demonstrated as a statistically significant greater reduction in the mean morphine consumption through 24 hours in patients who received CALDOLOR as compared to those receiving placebo (47 mg and 56 mg, respectively). The clinical relevance of this finding is supported by a greater reduction in pain intensity over 24 hours for patients treated with CALDOLOR, even though morphine was available on an as-needed basis.

In a study of patients who had undergone an elective abdominal or orthopedic surgery, 406 patients (87 men, 319 women) were randomized to receive CALDOLOR 400 mg, CALDOLOR 800 mg, or placebo administered every 6 hours (started intra-operatively), and morphine on an as-needed basis. This study failed to demonstrate a statistically significant difference in outcome between patients receiving CALDOLOR 800 mg or 400 mg and placebo, although there were trends favoring the active treatments.

An additional study of orthopedic surgical pain confirmed the findings of the study of abdominal surgical pain. A total of 185 patients were randomized and treated with CALDOLOR 800 mg or placebo administered every 6 hours (started pre-operatively) and morphine administered on an as-needed basis. Efficacy was demonstrated as a statistically significant greater reduction in pain intensity over 24 hours post-operatively for patients treated with CALDOLOR as compared to those receiving placebo.

14.2 Antipyretic (Fever)

The effect of CALDOLOR on fever was evaluated in two randomized, double-blind studies in adults and in one open-label study in pediatric patients.

In a multi-center study, 120 hospitalized patients (88 men, 32 women) with temperatures of 101°F or greater were randomized to CALDOLOR 400 mg, 200 mg, 100 mg or placebo, administered every 4 hours for 24 hours. Each of the three CALDOLOR doses, 100 mg, 200 mg, and 400 mg, resulted in a statistically greater percentage of patients with a reduced temperature (<101°F) after 4 hours, compared to placebo (65%, 73%, 77% and 32%, respectively). The dose response is shown in the figure below.

Figure 1: Temperature Reduction by Treatment Group, Hospitalized Febrile Patients

In a single-center study, 60 hospitalized patients (48 men, 12 women) with uncomplicated P. falciparum malaria having temperatures ≥100.4°F were randomized to CALDOLOR 400 mg or placebo, administered every 6 hours for 72 hours of treatment. There was a significant reduction in fever within the first 24 hours of treatment, measured as the area above the temperature 98.6°F vs. time curve for patients treated with CALDOLOR.

In a multi-center, open-label study, 100 hospitalized pediatric patients 6 months of age and older with temperatures of 101.0ºF or greater were randomized and treated with 10 mg/kg of CALDOLOR or a low dose of an active comparator every 4 hours as needed for fever.

Efficacy was demonstrated as a statistically significant greater reduction in temperature for the primary endpoint, an area under the curve analyses of temperature versus time for the first 2 hours, as well as over the entire dosing interval. Seventy-four percent of CALDOLOR treated patients became afebrile (temperature <99.5ºF) by the end of first dosing interval.

16 HOW SUPPLIED/STORAGE AND HANDLING

CALDOLOR (ibuprofen injection) is a clear, colorless, non-pyrogenic, aqueous solution supplied as follows:

800 mg/8 mL (100 mg/mL) single dose vial. Carton of 25 vials, NDC 66220-287-08.
800 mg/200 mL (4 mg/mL) single dose ready-to-use polypropylene flexible bag. Case of 20 bags, NDC 66220-284-22. Individual bag, NDC 66220-284-11.

Storage

Store at controlled room temperature 20 °C to 25 °C (68 °F to 77 °F); excursions permitted between 15 °C to 30 °C (59 °F to 86 °F) [see USP Controlled Room Temperature]. Discard the unused portion.

The stopper in the CALDOLOR vial does not contain natural rubber latex, dry natural rubber, or blends of natural rubber.

17 PATIENT COUNSELING INFORMATION

Advise the patient to read the FDA-approved patient labeling (Medication Guide) that accompanies each prescription dispensed. Patients, families, or their caregivers should be informed of the following information before initiating therapy with CALDOLOR and periodically during the course of ongoing therapy.

Cardiovascular Thrombotic Events

Advise patients to be alert for the symptoms of cardiovascular thrombotic events, including chest pain, shortness of breath, weakness, or slurring of speech, and to report any of these symptoms to their health care provider immediately [see Warnings and Precautions (5.1)].

Gastrointestinal Bleeding, Ulceration, and Perforation

Advise patients to report symptoms of ulcerations and bleeding, including epigastric pain, dyspepsia, melena, and hematemesis to their health care provider. In the setting of concomitant use of low-dose aspirin for cardiac prophylaxis, inform patients of the increased risk for and the signs and symptoms of GI bleeding [see Warnings and Precautions (5.2)].

Hepatotoxicity

Inform patients of the warning signs and symptoms of hepatotoxicity (e.g., nausea, fatigue, lethargy, pruritus, diarrhea, jaundice, right upper quadrant tenderness, and “flu-like” symptoms). If these occur, instruct patients to stop CALDOLOR and seek immediate medical therapy [see Warnings and Precautions (5.3)].

Heart Failure and Edema

Advise patients to be alert for the symptoms of congestive heart failure including shortness of breath, unexplained weight gain, or edema and to contact their healthcare provider if such symptoms occur [see Warnings and Precautions (5.5)].

Anaphylactic Reactions

Inform patients of the signs of an anaphylactic reaction (e.g., difficulty breathing, swelling of the face or throat). Instruct patients to seek immediate emergency help if these occur [see Contraindications (4) and Warnings and Precautions (5.7)].

Serious Skin Reactions including DRESS

Advise patients to stop taking CALDOLOR immediately if they develop any type of rash or fever and to contact their healthcare provider as soon as possible [see Warnings and Precautions (5.9, 5.10].

Female Fertility

Advise females of reproductive potential who desire pregnancy that NSAIDs, including CALDOLOR, may be associated with a reversible delay in ovulation [see Use in Specific Populations (8.3)]

Fetal Toxicity

Inform pregnant women to avoid use of CALDOLOR and other NSAIDs starting at 30 weeks gestation because of the risk of the premature closing of the fetal ductus arteriosus. If treatment with CALDOLOR is needed for a pregnant woman between about 20 to 30 weeks gestation, advise her that she may need to be monitored for oligohydramnios, if treatment continues for longer than 48 hours I [see Warnings and Precautions (5.10) and Use in Specific Populations (8.1)].

Avoid Concomitant Use of NSAIDs

Inform patients that the concomitant use of CALDOLOR with other NSAIDs or salicylates (e.g., diflunisal, salsalate) is not recommended due to the increased risk of gastrointestinal toxicity, and little or no increase in efficacy [see Warnings and Precautions (5.2) and Drug Interactions (7)]. Alert patients that NSAIDs may be present in “over the counter” medications for treatment of colds, fever, or insomnia.

Use of NSAIDS and Low-Dose Aspirin

Inform patients not to use low-dose aspirin concomitantly with CALDOLOR until they talk to their healthcare provider [see Drug Interactions (7)].

Manufactured for:
Cumberland Pharmaceuticals Inc.
Nashville, TN 37203
US Patent Number 6,727,286, 8,871,810, 8,735,452, 9,012,508, 9,072,661, 9,072,710, 9,114,068, 9,138,404, 9,295,639, and 9,649,284
CALDOLOR® is a registered trademark of Cumberland Pharmaceuticals Inc.

Principal Display Panel - 8 mL Vial Label

NDC 66220-287-08 Rx Only

Caldolor®
(ibuprofen) Injection

800 mg/8 mL

(100 mg/mL)

FOR INTRAVENOUS USE. MUST DILUTE BEFORE USE.

Store at controlled room temperature,
20°C - 25°C (68° - 77°F).

Single dose vial, discard unused portion.

DOSAGE: See package insert for dosage,
dilution, and administration information.

Principal Display Panel - 8 mL Carton Label

NDC 66220-287-08

25 x 8 mL Vials

800 mg/8 mL

For Intravenous Use

Must Dilute Before Use

Caldolor®
(ibuprofen) Injection

800 mg/8 mL

(100 mg/mL)

Principal Panel Display – Bag Label

200 mL NDC 66220-284-11

CALDOLOR ®

(ibuprofen) Injection

800 mg/200 mL (4 mg/mL)

Dosage:

For intravenous use.

See package insert for dosage information.

Use only if solution is clear.

Single dose container. Discard unused portion.

Store at controlled room temperature, 20°C-25°C (68°F-77°F)

Rx Only

Manufactured For:

CUMBERLAND ®

PHARMACEUTICALS

Nashville, TN, USA, 37203

Principal Panel Display – Case Label

CALDOLOR ®

(ibuprofen) Injection 800 mg/200 mL

(4 mg/mL)

Rx Only Contains 20 bags

Each bag contains 800 mg/200 mL ibuprofen in
an isosmotic pH 7.4 phosphate buffered sterile
injection solution.

See package insert for dosage information.

Single dose container. Discard unused portion.

LOT: EXP:

NDC 66220-284-22

Manufactured For:

CUMBERLAND ®

PHARMACEUTICALS

Nashville, TN, USA, 37203

Made in Spain

Store at controlled room temperature

20°C - 25°C (68°F - 77°F)